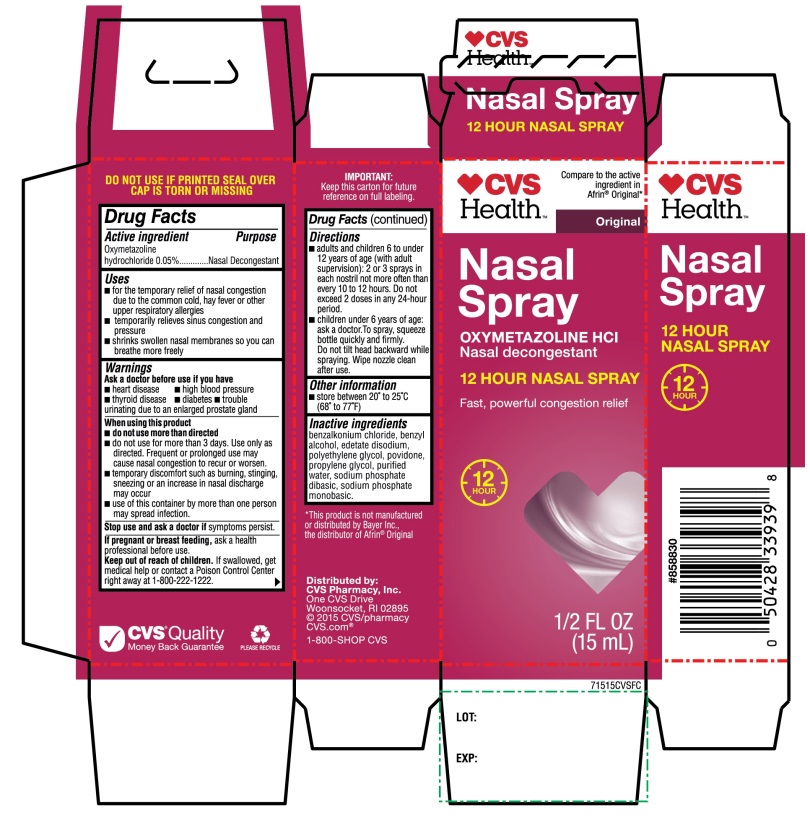 DRUG LABEL: CVS Health
NDC: 69842-575 | Form: SPRAY
Manufacturer: CVS Pharmacy,Inc.
Category: otc | Type: HUMAN OTC DRUG LABEL
Date: 20251209

ACTIVE INGREDIENTS: OXYMETAZOLINE HYDROCHLORIDE 0.05 g/100 mL
INACTIVE INGREDIENTS: BENZALKONIUM CHLORIDE; BENZYL ALCOHOL; EDETATE DISODIUM; POLYETHYLENE GLYCOL, UNSPECIFIED; POVIDONE, UNSPECIFIED; PROPYLENE GLYCOL; WATER; SODIUM PHOSPHATE, DIBASIC, ANHYDROUS; SODIUM PHOSPHATE, MONOBASIC, ANHYDROUS

CVS Health Nasal Spray OXYMETAZOLINE HCl 12 Hour Spray ½ FL OZ

Active ingredient

Oxymetazoline hydrochloride 0.05%

Purpose

Nasal Decongestant

Uses

- for the temporary relief of nasal congestion due to the common cold, hay fever or other upper respiratory allergies
- temporarily relieves sinus congestion and pressure
- shrinks swollen nasal membranes so you can breathe more freely

Warnings

Ask a doctor before use if you have

- heart disease
- high blood pressure
- thyroid disease
- diabetes
- trouble urinating due to an enlarged prostate gland

When using this product

- do not use more than directed
- do not use for more than 3 days. Use only as directed. Frequent and prolonged use may cause nasal congestion to recur and to worsen
- temporary discomfort such as burning, stinging, sneezing or an increase in nasal discharge may occur
- use of this container by more than one person may spread infection

Stop use and ask a doctor if

Symptoms persist.

If pregnant or breast-feeding,

ask a health professional before use.

Keep out of reach of children.

If swallowed, get medical help or contact a Poison Control Center right away at (1-800-222-1222)

Directions

- adults and children 6 to under 12 years of age (with adult supervision): 2 or 3 sprays in each nostril not more often than every 10 to 12 hours. Do not exceed 2 doses within any 24-hour period.
- children under 6 years of age: ask a doctor. To spray, squeeze bottle quickly and firmly. Do not tilt head backward while spraying. Wipe nozzle clean after use.

Other information

- store between 20°-25°C (68°-77°F)

Inactive ingredients

benzalkonium chloride, benzyl alcohol, edetate disodium, polyethylene glycol, povidone, propylene glycol ,purified water, sodium phosphate dibasic, sodium phosphate monobasic.

Principal Display Panel

CVS Health™

Compare to the active ingredient in Afrin® Original*

NDC 69842-575-15

Original

Nasal Spray

OXYMETAZOLINE HCl

Nasal decongestant

12 HOUR NASAL SPRAY

Fast, Powerful Congestion Relief

1/2 FL OZ (15 mL)

DO NOT USE IF PRINTED SEAL OVER CAP IS TORN OR MISSNG

IMPORTANT: Keep this carton for future reference on full labeling.

*This product is not manufactured or distributed by Bayer Inc., the distributor of Afrin®Original

Distributed by:

CVS Pharmacy, Inc.

One CVS Drive,

Woonsocket, RI 02895

© 2015 CVS/pharmacy

CVS.com®

1-800-SHOP CVS

CVS Quality

Money back Guarantee